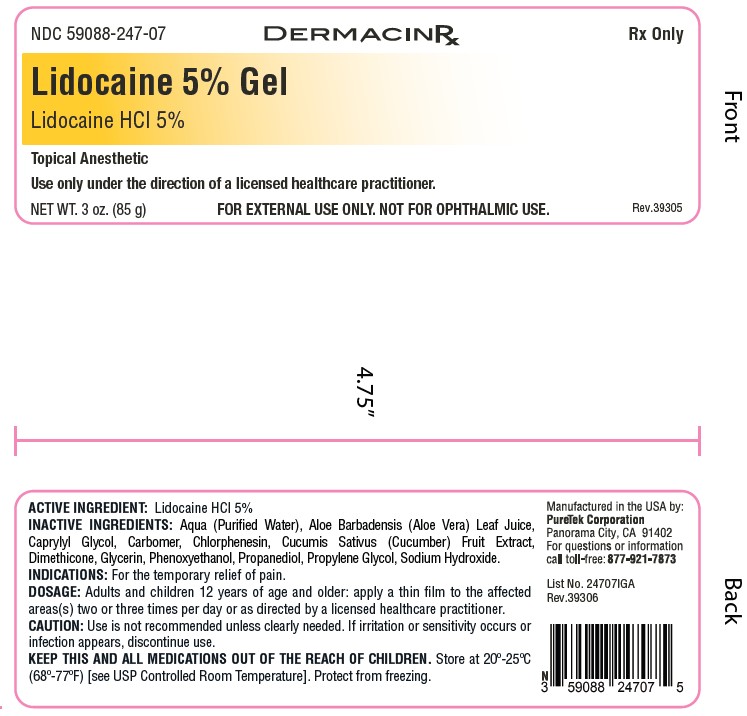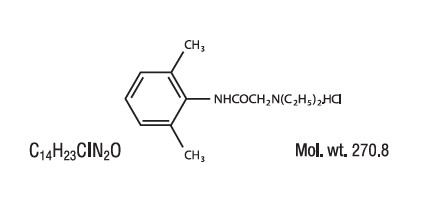 DRUG LABEL: Lidocaine 5% Gel
NDC: 59088-247 | Form: GEL
Manufacturer: Puretek Corporation
Category: prescription | Type: HUMAN PRESCRIPTION DRUG LABEL
Date: 20250919

ACTIVE INGREDIENTS: LIDOCAINE HYDROCHLORIDE 50 mg/1 g
INACTIVE INGREDIENTS: WATER; GLYCERIN; CARBOMER 940; PHENOXYETHANOL; CAPRYLYL GLYCOL; CUCUMBER; CHLORPHENESIN; PROPYLENE GLYCOL; ALOE VERA LEAF; PROPANEDIOL; DIMETHICONE; SODIUM HYDROXIDE

NDC 59088-247-07
Lidocaine 5% Gel
Lidocaine HCl 5%

DESCRIPTION

Lidocaine 5% Gel contains 50 mg of Lidocaine HCI per gram in a mild acidic vehicle with Aqua (Purified Water), Aloe Barbadensis (Aloe Vera) Leaf Juice, Caprylyl Glycol, Carbomer, Chlorphenesin, Cucumis Sativus (Cucumber) Fruit Extract, Dimethicone, Glycerin, Phenoxyethanol, Propanediol, Propylene Glycol, Sodium Hydroxide.

Lidocaine HCl is chemically designated as acetamide, 2-(diethylamino)-N-(2,6 dimethylphenyl), and has the following structure:

CLINICAL PHARMACOLOGY:

Mechanism of Action: Lidocaine 5% Gel releases lidocaine from a mild acidic vehicle to stabilize the neuronal membrane by inhibiting the ionic fluxes required for initiation and conduction of impulses, thereby effecting local anesthetic action. A mild acidic vehicle lowers pH to increase protection against alkaline irritants and to provide a favorable environment for healing.

Pharmacokinetics:

Lidocaine may be absorbed following topical administration to mucous membranes, its rate and extent of absorption depending upon the specific site of application, duration of exposure, concentration and total dosage. In general, the rate of absorption of local anesthetic agents following topical application occurs most rapidly after intratracheal administration. Lidocaine is also well-absorbed from the gastrointestinal tract, but little intact drug appears in the circulation because of biotransformation in the liver. Lidocaine is metabolized rapidly by the liver and metabolites and unchanged drug are excreted by the kidneys. Biotransformation includes oxidative N-dealkylation, ring hydroxylation, cleavage of the amide linkage and conjugation. N-dealkylation, a major pathway of biotransformation, yields the metabolites monoethylglycinexylidide and glycinexylidide. The pharmacological/ toxicological actions of these metabolites are similar to, but less potent than, those of lidocaine. Approximately 90% of lidocaine administered is excreted in the form of various metabolites and less than 10% is excreted unchanged. The primary metabolite in urine is a conjugate of 4-hydroxy-2, 6-dimethylaniline. The plasma binding of lidocaine is dependent on drug concentration and the fraction bound decreases with increasing concentration. At concentrations of 1 to 4 g of free base per mL, 60 to 80 percent of lidocaine is protein bound. Binding is also dependent on the plasma concentration of the alpha-1-acid glycoprotein. Lidocaine crosses the blood-brain and placental barriers, presumably by passive diffusion. Studies of lidocaine metabolism following intravenous bolus injections have shown that the elimination half-life of this agent is typically 1.5 to 2 hours. Because of the rapid rate at which lidocaine is metabolized, any condition that affects liver function may alter lidocaine kinetics. The half-life may be prolonged two-fold or more in patients with liver dysfunction. Renal dysfunction does not affect lidocaine kinetics, but may increase the accumulation of metabolites. Factors such as acidosis and the use of CNS stimulants and depressants affect the CNS levels of lidocaine required to produce overt systemic effects. Objective adverse manifestations become increasingly apparent with increasing venous plasma levels above 6 g free base per mL. In the rhesus monkey, arterial blood levels of 18-21 g/mL have been shown to be threshold for convulsive activity.

INDICATIONS:

For the temporary relief of pain.

CONTRAINDICATIONS:

Tuberculous or fungal lesions of skin vaccinia, varicella and acute herpes simplex and in persons who have shown hypersensitivity to any of its components. Lidocaine is contraindicated in patients with a known history of hypersensitivity to local anesthetics of the amide type.

WARNINGS:

For external use only. Not for ophthalmic use.

PRECAUTIONS:

If irritation or sensitivity occurs or infection appears, discontinue use and institute appropriate therapy. Lidocaine 5% Gel should be used with caution in ill, elderly, debilitated patients and children who may be more sensitive to the systemic effects of lidocaine.

Carcinogenesis, Mutagenesis and Impairment of Fertility:

Studies of lidocaine in animals to evaluate the carcinogenic and mutagenic potential of the effect on fertility have not been conducted.

Use in Pregnancy:

Teratogenic Effects; Pregnancy Category B. Reproduction studies have been performed for lidocaine in rats at doses up to 6.6 times the human dose and have revealed no evidence of harm to the fetus caused by lidocaine. There are, however, no adequate and well-controlled studies in pregnant women. Animal reproduction studies are not always predictive of human response. General consideration should be given to this fact before administering lidocaine to women of childbearing potential, especially during early pregnancy when maximum organogenesis takes place.

Nursing Mothers:

It is not known whether this drug is excreted in human milk. Because many drugs are excreted in human milk, caution should be exercised when this drug is administered to a nursing mother.

Pediatric Use:

Dosage in pediatric patients would be reduced commensurate with age, body weight and physical condition.

ADVERSE REACTIONS:

During or immediately after treatment, the skin at the site of treatment may develop erythema or edema or may be the locus of abnormal sensation.

DOSAGE:

Adults and children 12 years of age and older: apply a thin film to the affected areas(s) two or three times per day or as directed by a licensed healthcare practitioner.

HOW SUPPLIED:

Lidocaine 5% Gel is supplied in a 3 oz. (85 g) tube with CRC cap (NDC 59088-247-07).

KEEP THIS AND ALL MEDICATIONS OUT OF THE REACH OF CHILDREN.
Store at 20º-25ºC (68º-77º F) [see USP Controlled Room Temperature]. Protect from freezing.

LABEL

Manufactured by:
PureTek Corporation
Panorama City, CA 91402
For questions or information call toll-free: 877-921-7873